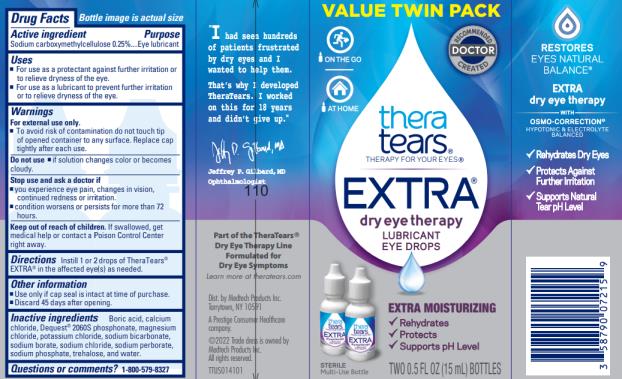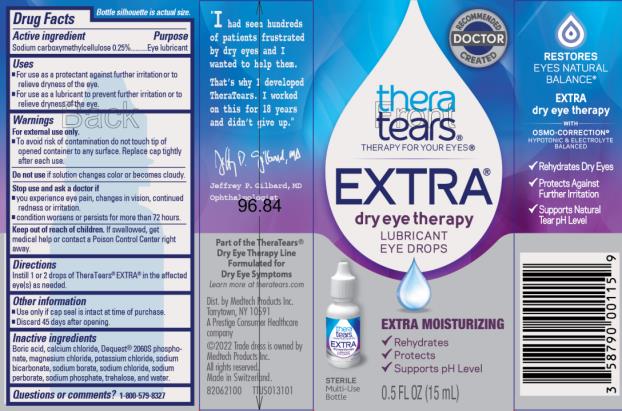 DRUG LABEL: TheraTears Extra
NDC: 58790-007 | Form: SOLUTION/ DROPS
Manufacturer: MEDTECH PRODUCTS INC
Category: otc | Type: HUMAN OTC DRUG LABEL
Date: 20241213

ACTIVE INGREDIENTS: Carboxymethylcellulose Sodium, Unspecified Form 2.5 mg/1 mL
INACTIVE INGREDIENTS: Boric Acid; calcium chloride; Diethylenetriamine Pentamethylene Phosphonic Acid; potassium chloride; sodium bicarbonate; sodium borate; sodium chloride; magnesium chloride; sodium perborate; sodium phosphate; trehalose; water

TheraTears Extra MD 58790-007

Drug Facts

Active ingredient

Sodium carboxymethylcellulose 0.25%

Purpose

Eye lubricant

Uses

- For use as a protectant against further irritation or to relieve dryness of the eye.
- For use as a lubricant to prevent further irritation or to relieve dryness of the eye.

Warnings

For external use only

- To avoid risk of contamination do not touch tip of opened container to any surface. Replace cap tightly after each use.

Do not use

- if solution changes color or becomes cloudy.

Stop use and ask a doctor if

- you experience eye pain, changes in vision, continued redness or irritation.
- condition worsens or persists for more than 72 hours.

Keep out of reach of children.

If swallowed, get medical help or contact a Poison Control Center right away.

Directions

Instill 1 or 2 drops of TheraTears® Extra® in the affected eye(s) as needed.

Other information

- Do not use if neck ring is broken or missing.
- Discard 45 days after opening.

Inactive ingredients

Boric acid, calcium chloride, Dequest®, 2060S phosphonate, magnesium chloride, potassium chloride, sodium bicarbonate, sodium borate, sodium chloride, sodium perborate, sodium phosphate, trehalose, and water for injection.

Questions or comments?

1-800-579-8327

Principal Display Panel Text for Container Label:

thera

tears®

THERAPY FOR YOUR EYES®

EXTRA®

dry eye therapy

LUBRICANT

EYE DROPS

EXTRA MOISTURIZING

√ Rehydrates

√ Protects

√ Supports pH Level

STERILE

Multi-Use

Bottle TWO 0.5 FL OZ (15 mL) BOTTLES

Principal Display Panel Text for Carton Label:

RECOMMENDED

DOCTOR

CREATED

thera

tears®

THERAPY FOR YOUR EYES®

EXTRA®

dry eye therapy

LUBRICANT

EYE DROPS

EXTRA MOISTURIZING

√ Rehydrates

√ Protects

√ Supports pH Level

STERILE

Multi-Use

Bottle 0.5 FL OZ (15 mL)